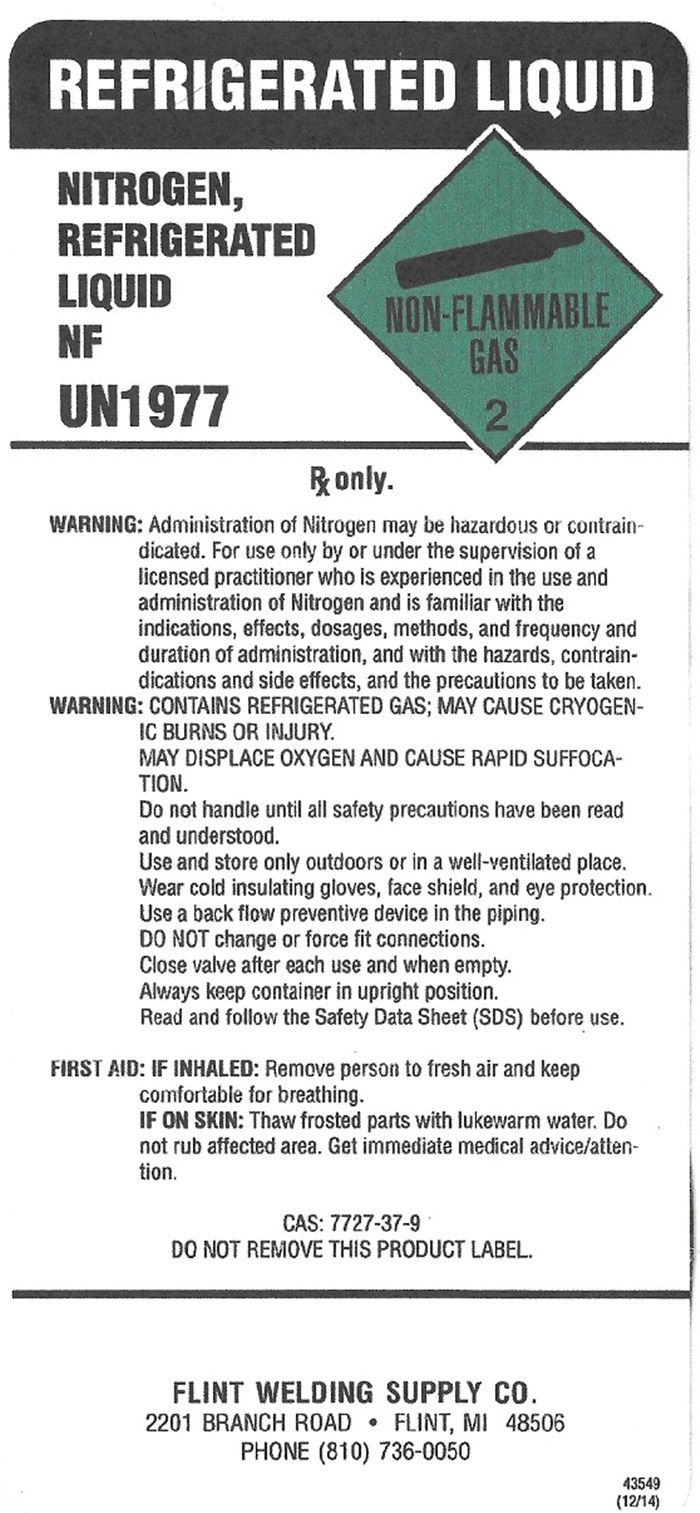 DRUG LABEL: NITROGEN
NDC: 10412-0095 | Form: GAS
Manufacturer: Flint Welding Supply Company
Category: prescription | Type: HUMAN PRESCRIPTION DRUG LABEL
Date: 20251013

ACTIVE INGREDIENTS: NITROGEN 99.5 L/100 L

Nitrogen

NITROGEN REFRIGERATED LIQUID NF

REFRIGERATED LIQUID

NITROGEN, REFRIGERATED LIQUID NF UN1977 NON-FLAMMABLE GAS 2

Rx only.

WARNING: Administration of Nitrogen may be hazardous or contraindicated. For use only by or under the supervision of a licensed practitioner who is experienced in the use and administration of Nitrogen and is familiar with the indications, effects, dosages, methods, and frequency and duration of administration, and with the hazards, contraindications, and side effects, and the precautions to be taken.

WARNING: CONTAINS REFRIGERATED GAS; MAY CAUSE CRYOGENIC BURNS OR INUURY. MAY DISPLACE OXYGEN AND CAUSE RAPID SUFFOCATION. Do not handle until all safety precautions have been read and understood. Use and store only outdoors or in a well-ventilated place. Wear cold insulating gloves, face shield, and eye protection. Use a back flow preventive device in the piping. DO NOT change or force fit connections. Close valve after each use and when empty. Always keep container in upright position. Read and follow the Safety Data Sheet (SDS) before use.

FIRST AID: IF INHALED: Remove person to fresh air and keep comfortable for breathing. IF ON SKIN: Thaw frosted parts with lukewarm water. Do not rub affected area. Get immediate medical advice/attention.

CAS: 7727-37-9

DO NOT REMOVE THIS PRODUCT LABEL.

FLINT WELDING SUPPLY CO.

2201 BRANCH ROAD • FLINT, MI 48506

PHONE (810) 736-0050

43549(12/14)